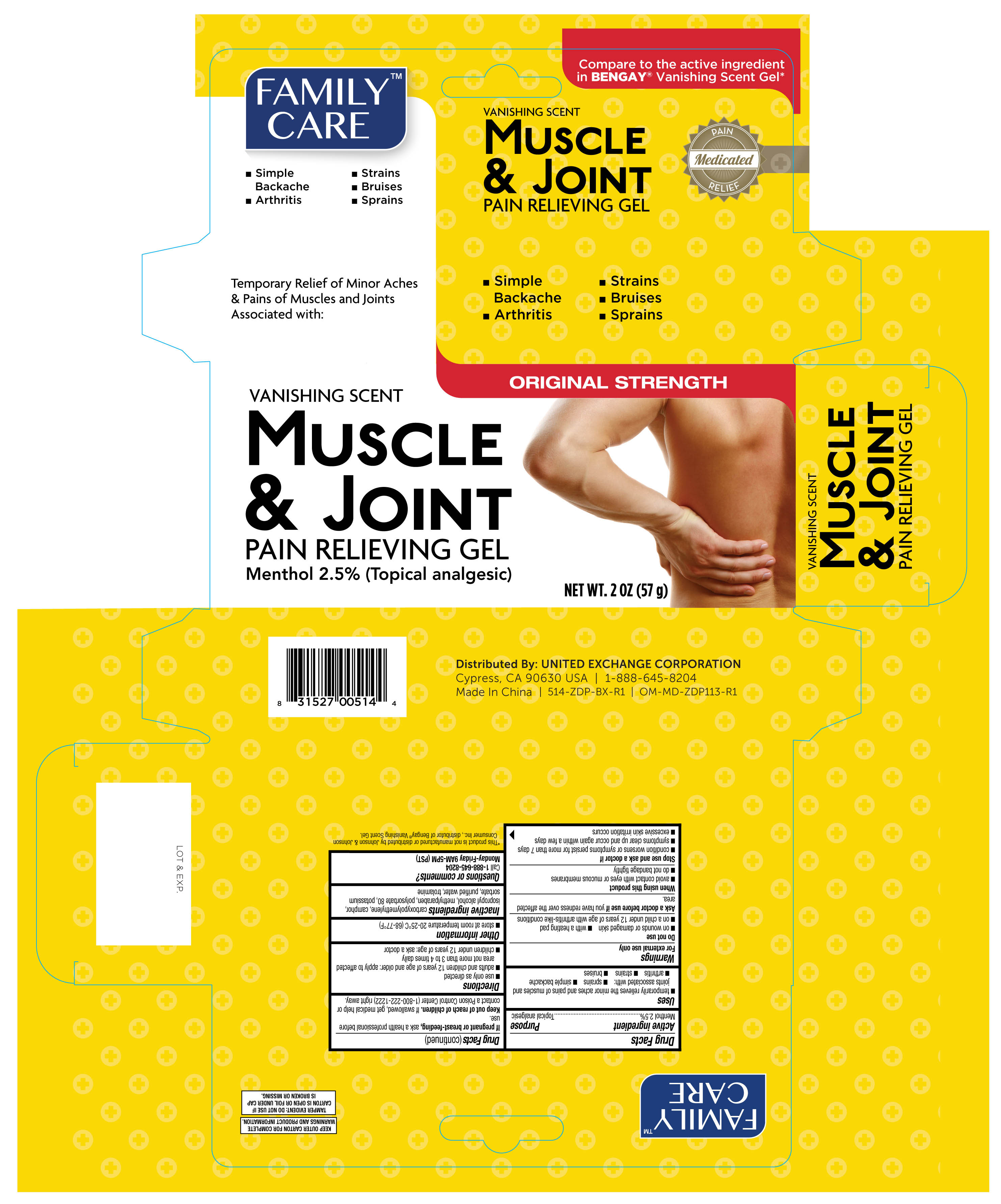 DRUG LABEL: Family Care Muscle and Joint
NDC: 65923-144 | Form: GEL
Manufacturer: United Exchange Corp.
Category: otc | Type: HUMAN OTC DRUG LABEL
Date: 20251030

ACTIVE INGREDIENTS: MENTHOL, UNSPECIFIED FORM 25 mg/1 g
INACTIVE INGREDIENTS: CAMPHOR (SYNTHETIC); TROLAMINE; METHYLPARABEN; POLYSORBATE 80; POTASSIUM SORBATE; WATER; CARBOXYPOLYMETHYLENE; ISOPROPYL ALCOHOL

Family Care Muscle & Joint Pain Relieving Gel 2 oz 514 ZDP

Active ingredient Purpose

Menthol 2.5%.................................................................Topical analgesic

Uses

- temporarily relieves the minor aches and pains of muscles and joints associated with:
- sprains
- simple backache
- arthritis
- strains
- bruises

Warnings

For external use only

Do not use

- on wounds or damaged skin
- with a heating pad
- on a child under 12 years of age with arthritis-like conditions

Ask a doctor before use if you have redness over the affected area.

When using this product

- avoid contact with eyes or mucous membranes
- do not bandage tightly

Stop use and ask a doctor if

- condition worsens or symptoms persist for more than 7 days
- symptoms clear up and occur again within a few days
- excessive skin irritation occurs

PREGNANCY OR BREAST FEEDING

If pregnant or breast-feeding, ask a health professional before use.

Keep out of reach of children. If swallowed, get medical help or contact a Poison Control Center (1-800-222-1222) right away.

Directions

- use only as directed
- adults and children 12 years of age and older: apply to affected area not more than 3 to 4 times daily
- children under 12 years of age: ask a doctor

Other information

- store at room temperature 20-25°C (68-77°F)

Inactive ingredients

carboxypolymethylene, camphor isopropyl alcohol, methylparaben, polysorbate 80, potassium sorbate, purified water, trolamine

DOSAGE AND ADMINISTRATION

Distributed by:

United Exchange Corp.

Cypress, CA 90630 USA

Made in China